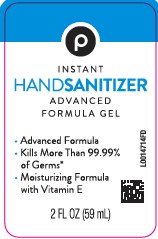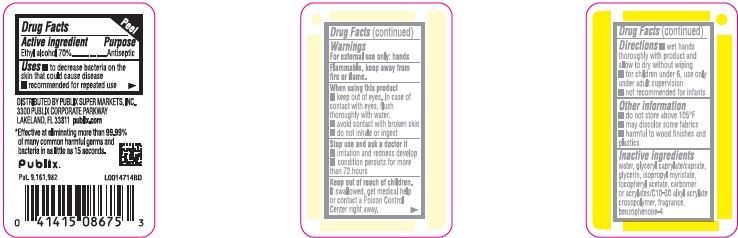 DRUG LABEL: Advanced Hand Sanitizer
NDC: 56062-370 | Form: GEL
Manufacturer: Publix Super Markets, Inc.
Category: otc | Type: HUMAN OTC DRUG LABEL
Date: 20260205

ACTIVE INGREDIENTS: ALCOHOL 70 mL/100 mL
INACTIVE INGREDIENTS: WATER; GLYCERYL CAPRYLATE/CAPRATE; GLYCERIN; ISOPROPYL MYRISTATE; .ALPHA.-TOCOPHEROL ACETATE; CARBOMER COPOLYMER TYPE B (ALLYL PENTAERYTHRITOL CROSSLINKED); SULISOBENZONE

Publix 370.001/370AE rev 1
Advanced Hand Sanitizer

Active Ingredient

Ethyl alcohol 70%

Purpose

Antiseptic

Uses

- to decrease bacteria on the skin that could cause disease
- recommended for repeated use

Warnings

For external use only: hands

Flammable, keep away from fire or flame.

When using this product

- keep out of eyes. In case of contact with eyes, flush thoroughly with water.
- avoid contact with broken skin
- do not inhale or ingest

Stop use and ask a doctor if

- irritation and redness develop
- condition persists for more than 72 hours

Keep out of reach of children.

If swallowed, get medical help or contact a Poison Control Center right away.

Directions

- wet hands thoroughly with product and allow to dry without wiping
- for children under 6, use only under adult supervision
- not recommended for infants

Other information

- do not store above 105⁰ F
- may discolor some fabrics
- harmful to wood finishes and plastics

Inactive ingredients

water, glyceryl caprylate/caprate, glycerin, isopropyl myristate, tocopheryl acetate, acrylates/C10-30 alkyl acrylate crosspolymer, fragrance, benzophenone-4

ADVERSE REACTION

DISTRIBUTED BY PUBLIX SUPER MARKETS, INC.,

3300 PUBLIX CORPORATE PARKWAY

LAKELAND, FL 33811

publix.com

Publix

Pat. 9,161,982

Claim

*Effective at eliminating more than 99.99% of many common harmful germs and bacteria in as little as 15 seconds.

principal display panel

P

Instant

HANDS ANITIZER

ADVANCED FORMULA GEL

- Advanced Formula
- Kills more than 99.99% of germs*
- Moisturizing Formula with Vitamin E

2 FL OZ (59 mL)